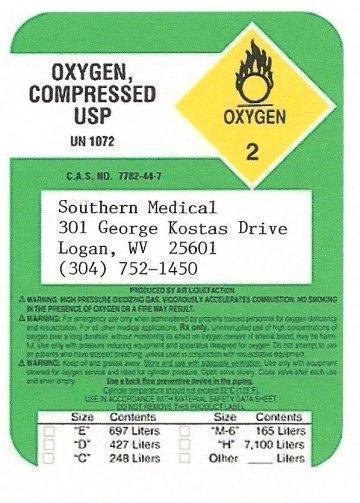 DRUG LABEL: Southern Medical Oxygen, Compressed
NDC: 53199-100 | Form: GAS
Manufacturer: Michael R. Mullins II Inc. dba Southern Medical
Category: prescription | Type: HUMAN PRESCRIPTION DRUG LABEL
Date: 20191226

ACTIVE INGREDIENTS: OXYGEN 1 L/1 L

Michael R. Mullins II dba Southern Medical Compressed Oxygen

PACKAGE LABEL

OXYGEN, COMPRESSED USP
UN1072

Southern Medical
301 George Kostas Drive
Logan, WV 25601
(304) 752-1450
Produced by Air Liquefaction.
WARNING: HIGH PRESSURE OXIDIZING GAS VIGOROUSLY ACCELERATES COMBUSTION. No smoking
in the presence of oxygen or a fire may result.

WARNING: For emergency use only when administered by properly trained personnel for oxygen deficiency
and resuscitation. For all other medical applications, Rx only. Uninterrupted use of high concentrations of oxygen over a long duration, without
monitoring its effect on oxygen content of arterial blood, may be harmful. Do not attempt to use on patients who have stopped
breathing unless used in conjunction with resuscitation equipment

WARNING: Keep oil and grease away. Store and use with adequate ventilation. Use only with equipment
cleaned for oxygen service and rated for cylinder pressure. Open valve slowly. Close valve after each use and when empty.

Use a back flow prevention device in the piping.

Cylinder temperature should not exceed 52C (125F).

Use in accordance with the Material Safety Data Sheet.
Do not remove this product label.